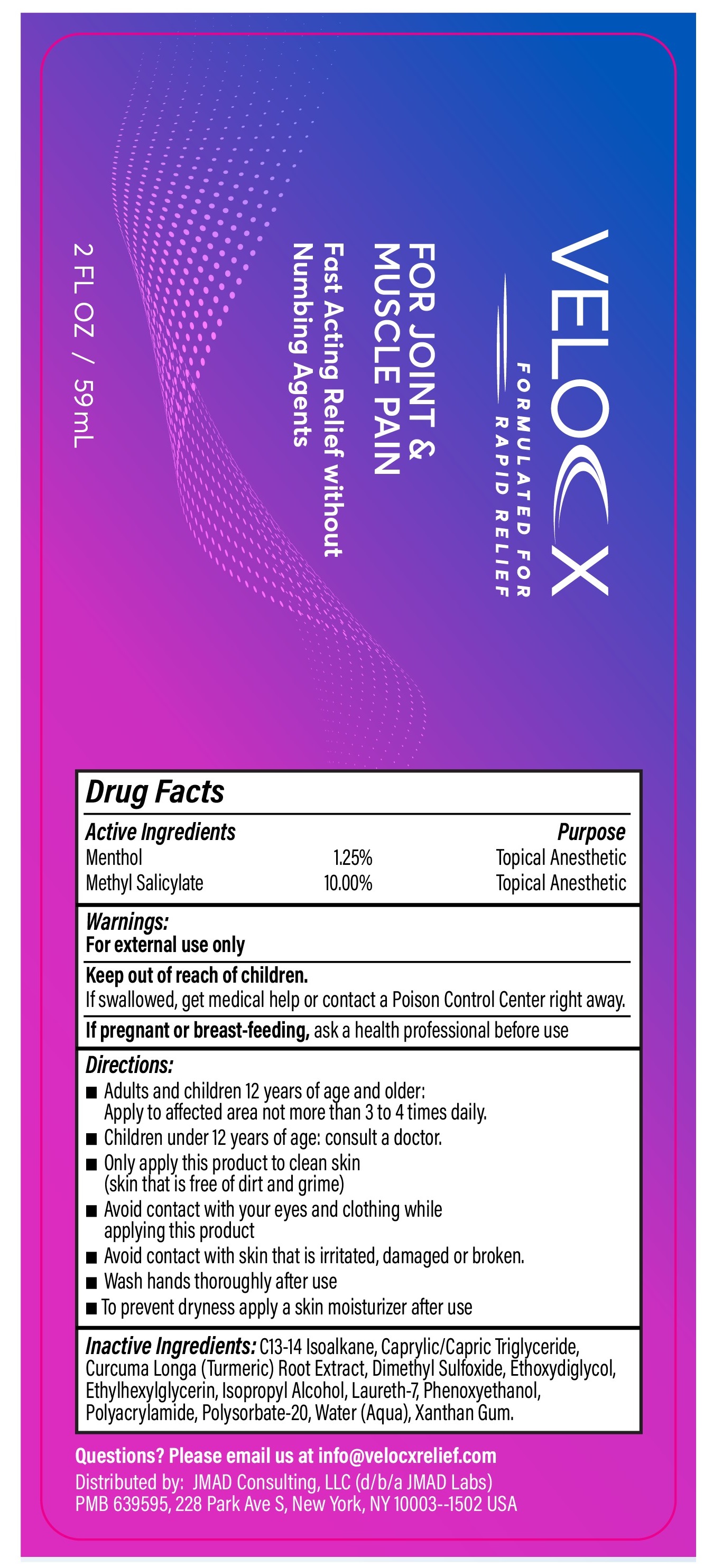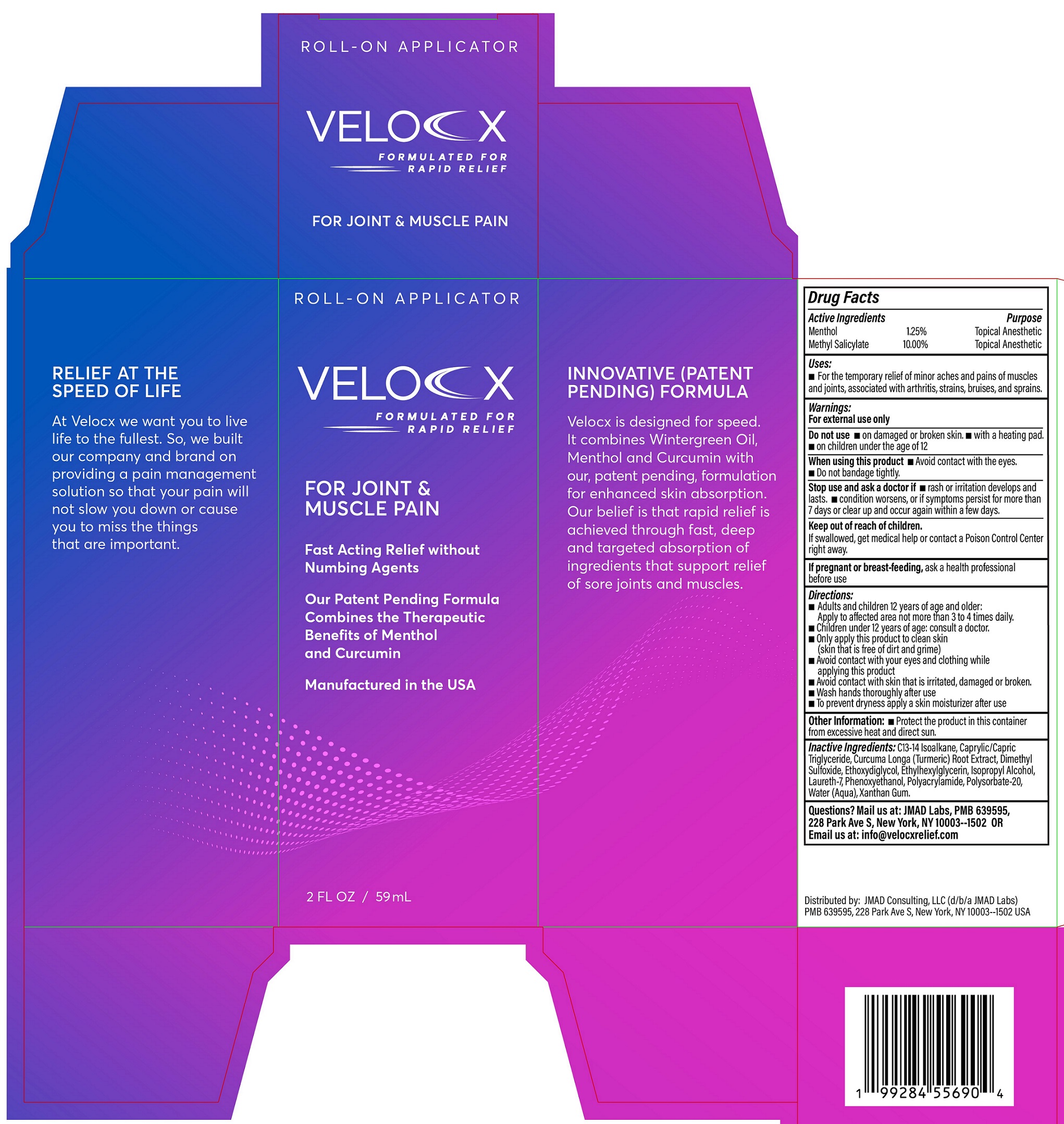 DRUG LABEL: Velocx for Joint and Muscle Pain Roll-On Applicator
NDC: 87340-982 | Form: SOLUTION
Manufacturer: JMAD Consulting LLC, dba JMAD Labs
Category: otc | Type: HUMAN OTC DRUG LABEL
Date: 20260126

ACTIVE INGREDIENTS: MENTHOL 12.5 mg/1 mL; METHYL SALICYLATE 100 mg/1 mL
INACTIVE INGREDIENTS: C13-14 ISOPARAFFIN; MEDIUM-CHAIN TRIGLYCERIDES; TURMERIC; DIMETHYL SULFOXIDE; ETHYLENE GLYCOL MONOETHYL ETHER; ETHYLHEXYLGLYCERIN; ISOPROPYL ALCOHOL; LAURETH-7; PHENOXYETHANOL; POLYSORBATE 20; WATER; XANTHAN GUM

Velocx for Joint & Muscle Pain Roll-On Applicator

Active Ingredients

Menthol 1.25%
Methyl Salicylate 10.00%

Purpose

Topical Anesthetic

Uses:

- For the temporary relief of minor aches and pains of muscles and joints, associated with arthritis, strains, bruises, and sprains.

Warnings:

For external use only

Do not use

- on damaged or broken skin.
- with a heating pad.
- on children under the age of 12

When using this product

- Avoid contact with the eyes.
- Do not bandage tightly.

Stop use and ask a doctor if

- rash or irritation develops and lasts.
- condition worsens, or if symptoms persist for more than 7 days or clear up and occur again within a few days.

Keep out of reach of children.

If swallowed, get medical help or contact a Poison Control Center right away.

If pregnant or breast-feeding,

ask a health professional before use

Directions:

- Adults and children 2 years of age and older: Apply to affected area not more than 3 to 4 times daily.
- Children under 2 years of age: consult a doctor.
- Only apply this product to clean skin (skin that is free of dirt and grime)
- Avoid contact with your eyes and clothing while applying this product
- Avoid contact with skin that is irritated, damaged or broken.
- Wash hands thoroughly after use
- To prevent dryness apply a skin moisturizer after use

Other information:

- Protect the product in this container from excessive heat and direct sun.

Inactive Ingredients:

C13-14 Isoalkane, Caprylic/Capric Triglyceride, Curcuma Longa (Turmeric) Root Extract, Dimethyl Sulfoxide, Ethoxyethanol, Ethylhexylglycerin, Isopropyl Alcohol, Laureth-7, Phenoxyethanol, Polyacrylamide, Polysorbate-20, Water (Aqua), Xanthan Gum.

Questions?

Email us at: info@velocxrelief.com